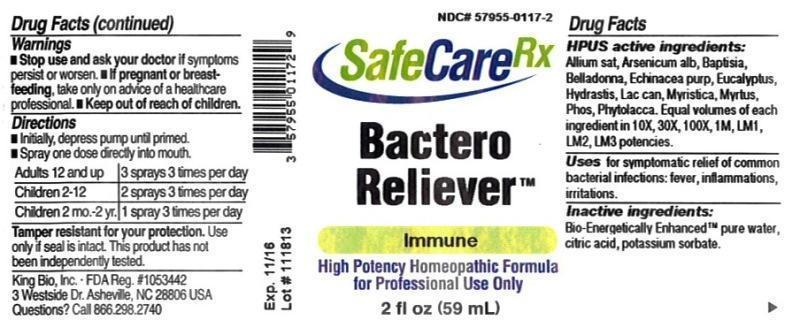 DRUG LABEL: Bactero Reliever
NDC: 57955-0117 | Form: LIQUID
Manufacturer: King Bio Inc.
Category: homeopathic | Type: HUMAN OTC DRUG LABEL
Date: 20150223

ACTIVE INGREDIENTS: GARLIC 10 [hp_X]/59 mL; ARSENIC TRIOXIDE 10 [hp_X]/59 mL; BAPTISIA TINCTORIA ROOT 10 [hp_X]/59 mL; ATROPA BELLADONNA 10 [hp_X]/59 mL; ECHINACEA PURPUREA 10 [hp_X]/59 mL; EUCALYPTUS GLOBULUS LEAF 10 [hp_X]/59 mL; GOLDENSEAL 10 [hp_X]/59 mL; CANIS LUPUS FAMILIARIS MILK 10 [hp_X]/59 mL; VIROLA SEBIFERA RESIN 10 [hp_X]/59 mL; MYRTUS COMMUNIS TOP 10 [hp_X]/59 mL; PHOSPHORUS 10 [hp_X]/59 mL; PHYTOLACCA AMERICANA ROOT 10 [hp_X]/59 mL
INACTIVE INGREDIENTS: WATER; ANHYDROUS CITRIC ACID; POTASSIUM SORBATE

Bactero Reliever™

ACTIVE INGREDIENT

Drug Facts__________________________________________________________________________________________________________

HPUS active ingredients: Allium sativum, Arsenicum album, Baptisia tinctoria, Belladonna, Echinacea purpurea, Eucalyptus globulus, Hydrastis canadensis, Lac caninum, Myristica sebifera, Myrtus communis, Phosphorus, Phytolacca decandra. Equal volumes of each ingredient in 10X, 30X, 100X, 1M, LM1, LM2, LM3 potencies.

INDICATIONS AND USAGE

Uses for symptomatic relief of common bacterial infections: fever, inflammations, irritations.

Inactive Ingredients:

Bio-Energetically Enhanced™ pure water, citric acid and potassium sorbate.

Warnings

- Stop use and ask your doctor if symptoms persist or worsen.
- If pregnant or breast-feeding, take only on advice of a healthcare professional.

- Keep out of reach of children.

Directions

- Initially, depress pump until primed.
- Spray one dose directly into mouth.
- Adults 12 and up: 3 sprays 3 times per day
- Children 2-12: 2 sprays 3 times per day
- Children 2mo-2yr.: 1 spray 3 times per day

OTHER SAFETY INFORMATION

Tamper resistant for your protection. Use only if safety seal is intact. This product has not been independently tested.

PURPOSE

Uses for symptomatic relief of common bacterial infections:

- fever
- inflammations
- irritations